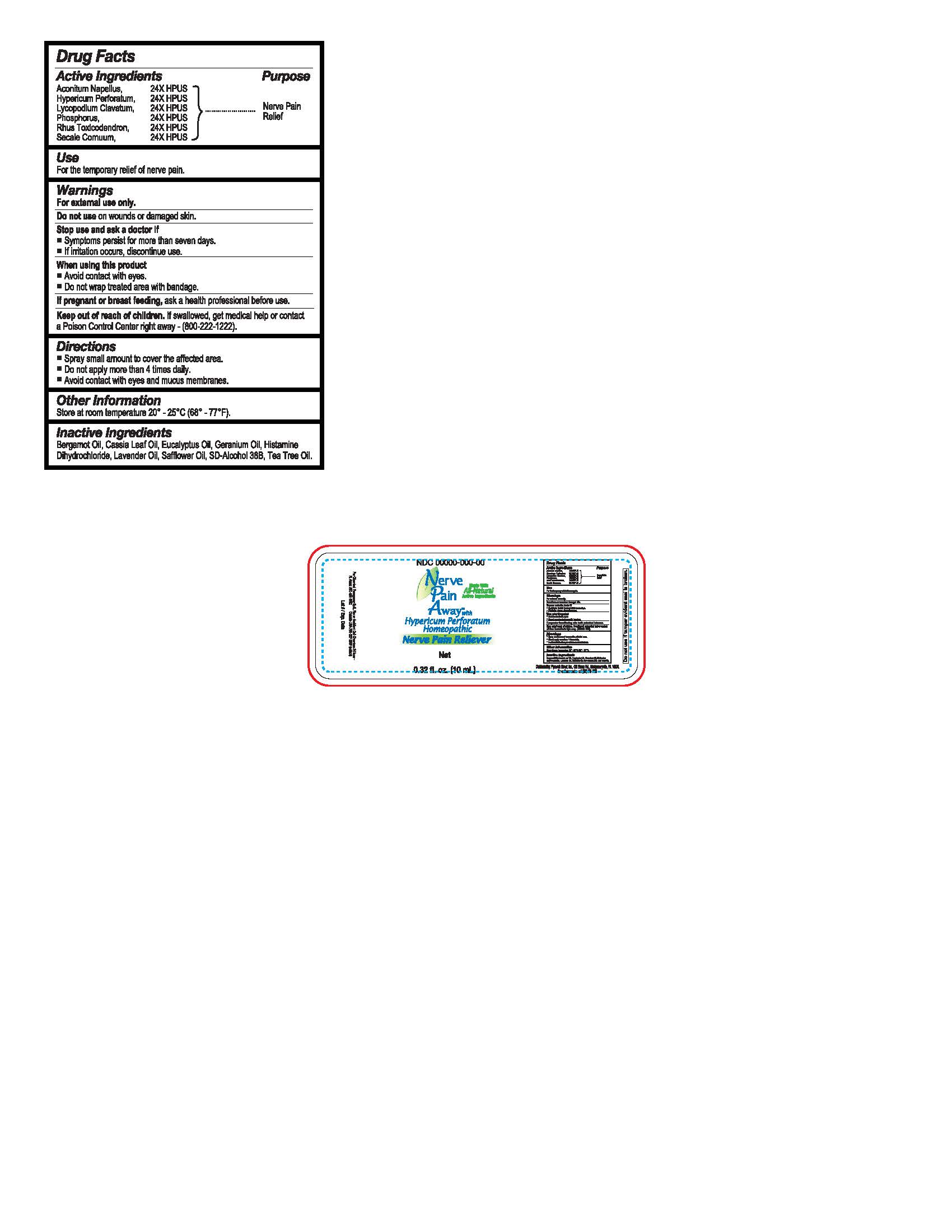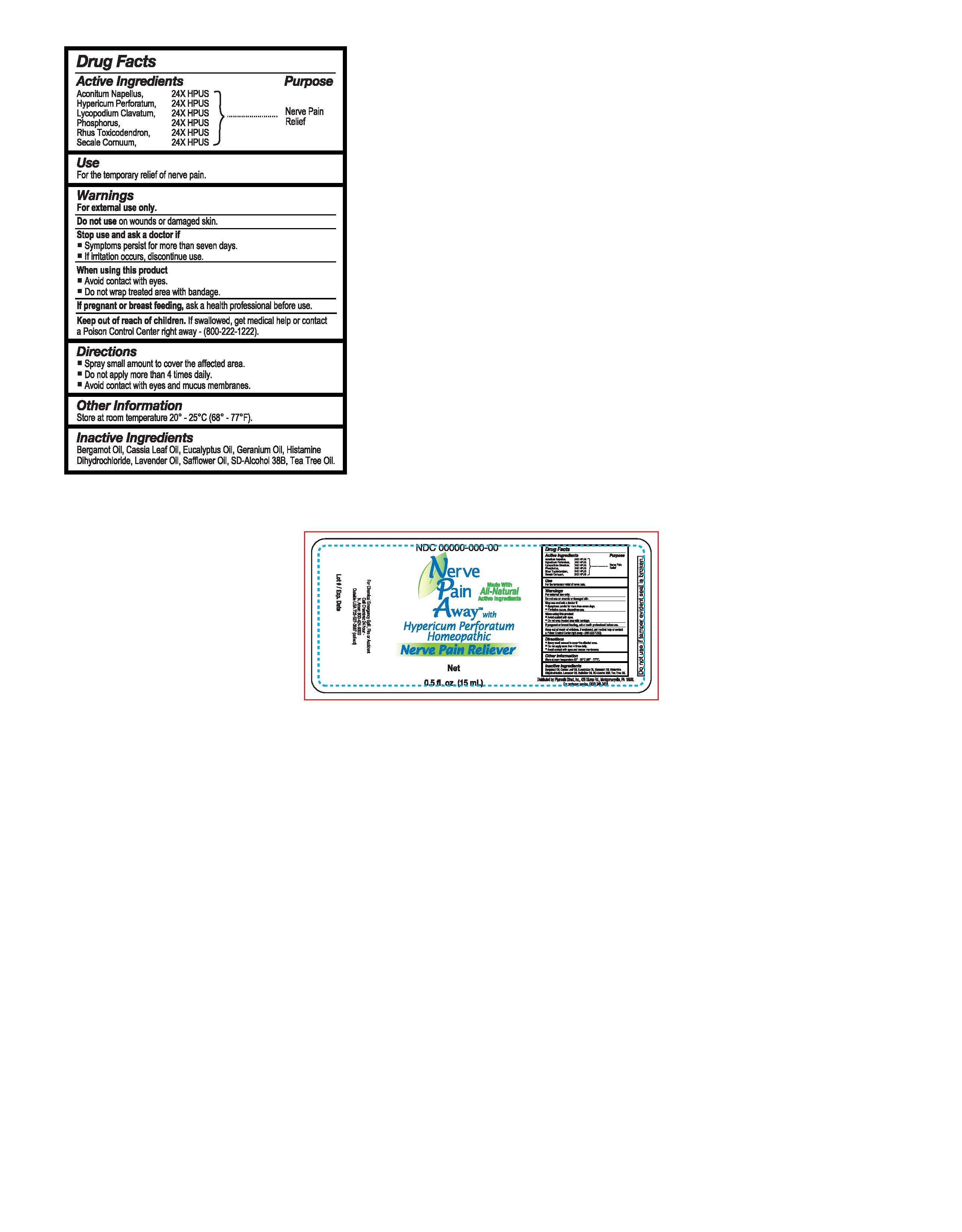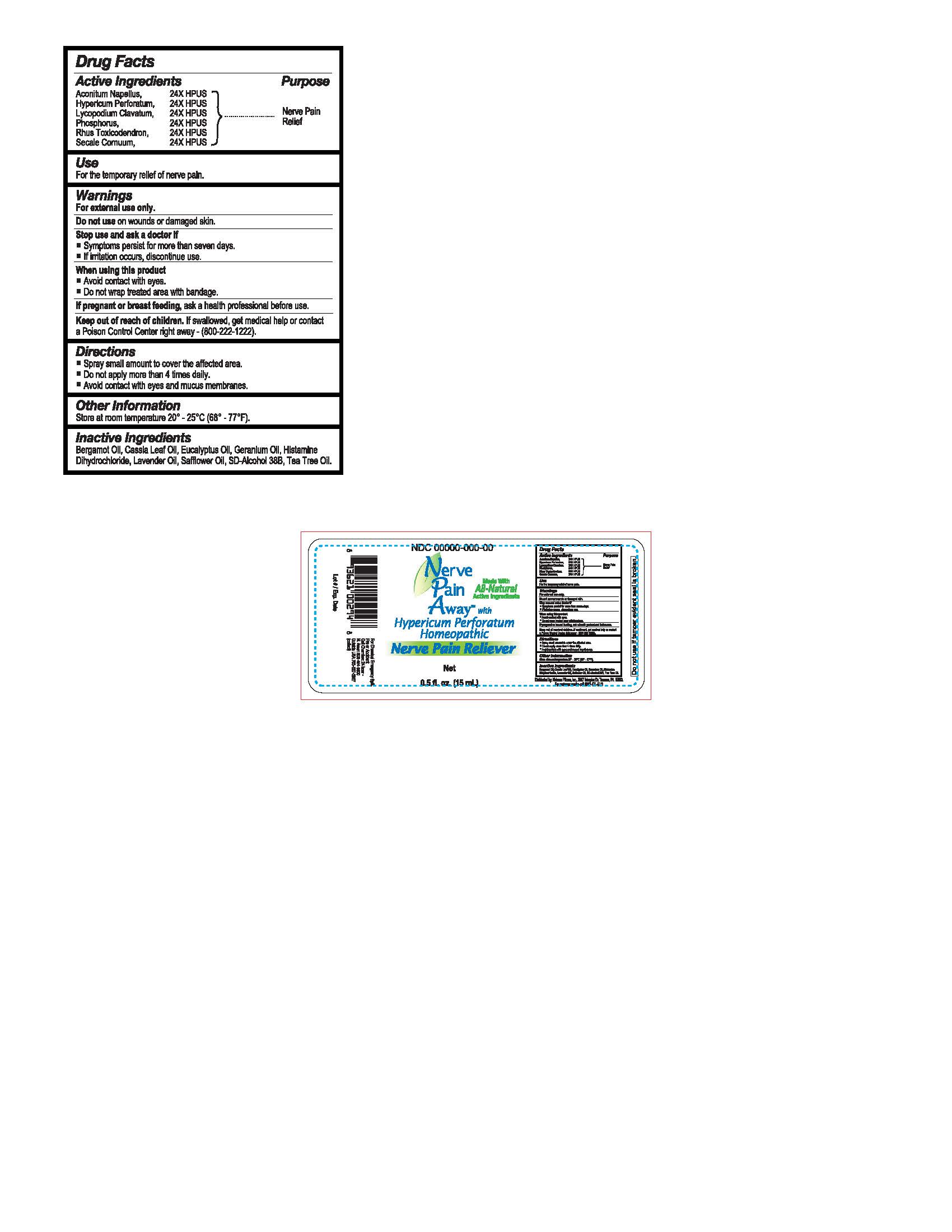 DRUG LABEL: Pain Away Solution
NDC: 65121-887 | Form: SPRAY
Manufacturer: Pure Source, LLC
Category: homeopathic | Type: HUMAN OTC DRUG LABEL
Date: 20170825

ACTIVE INGREDIENTS: HYPERICUM PERFORATUM 24 [hp_X]/100 mL; LYCOPODIUM CLAVATUM SPORE 24 [hp_X]/100 mL; ACONITUM NAPELLUS 24 [hp_X]/100 mL; PHOSPHORUS 24 [hp_X]/100 mL; TOXICODENDRON PUBESCENS LEAF 24 [hp_X]/100 mL; CLAVICEPS PURPUREA SCLEROTIUM 24 [hp_X]/100 mL
INACTIVE INGREDIENTS: EUCALYPTUS OIL; LAVENDER OIL; TEA TREE OIL; GERANIUM OIL, ALGERIAN TYPE; CHINESE CINNAMON LEAF OIL; BERGAMOT OIL; SAFFLOWER OIL; HISTIDINE MONOHYDROCHLORIDE; ALCOHOL

ACTIVE INGREDIENT

Aconitum Napellus, 24X HPUS

Hypericum Peforatum, 24X HPUS

Lycopodium Clavatum, 24X HPUS

Phosphorus, 24X HPUS

Rhus Toxicodendron, 24X HPUS

Secale Cornuum, 24X HPUS

PURPOSE

Nerve Pain Relief

Keep out of reach of children. If swallowed, get medical help or contact a Poison Control Center right away - (800-222-1222)

Use

For the temporary relief of nerve pain

Warnings

For external use only.

Do not use on wounds or damaged skin.

Stop use and ask doctor if

- Symptoms persist for more than seven days.
- If irritation occurs, discontinue use.

When using this product

- Avoid contact with eyes.
- Do not wrap treated area with bandage.

If pregnant or breast feeding, ask a health professional before use.

Directions

- Spray small amount to cover the affected area.
- Do not apply more than 4 times daily.
- Avoid contact with eyes and mucus membranes.

Inactive Ingredients

Bergamot Oil, Cassia Leaf Oil, Eucalyptus Oil, Geranium Oil, Histamine Dihydrochloride, Lavender Oil, Safflower Oil, SD-Alcohol 38B, Tea Tree Oil